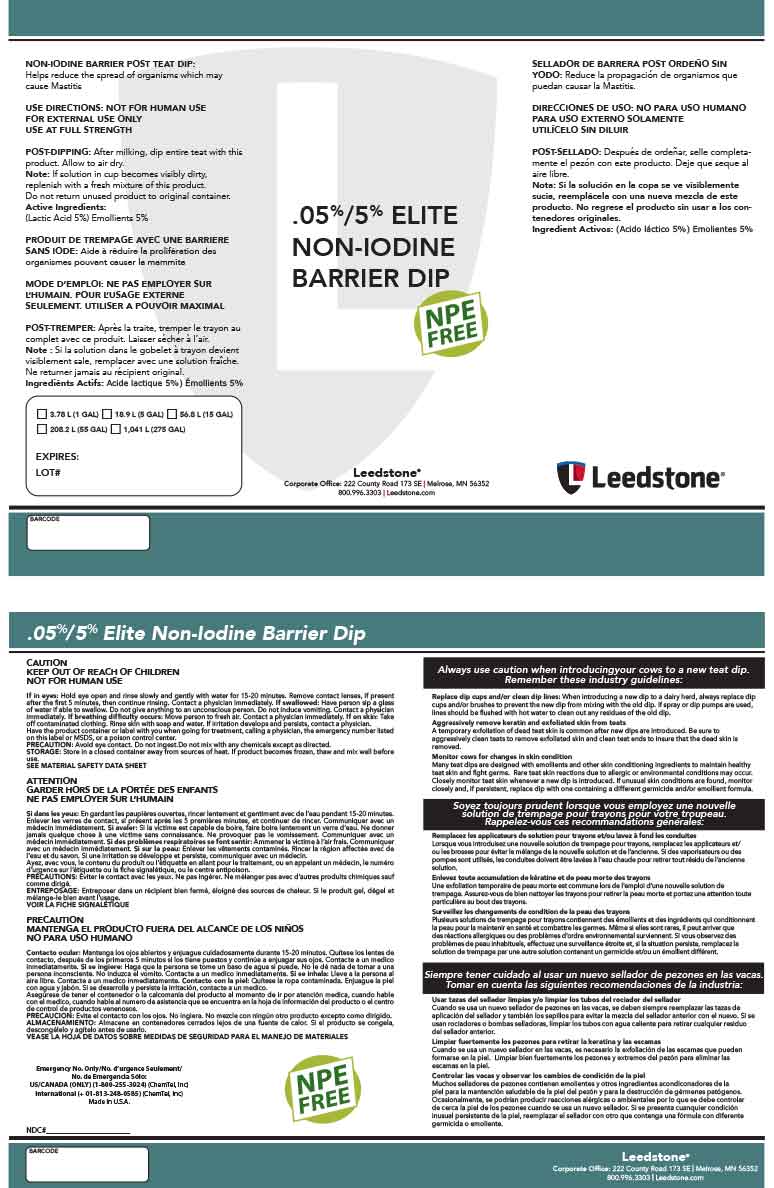 DRUG LABEL: 05%/5% Elite Barrier Dip
NDC: 48106-2044 | Form: LIQUID
Manufacturer: BOUMATIC, LLC
Category: animal | Type: OTC ANIMAL DRUG LABEL
Date: 20221202

ACTIVE INGREDIENTS: LACTIC ACID 5 g/100 g
INACTIVE INGREDIENTS: GLYCERIN 2 g/100 g; SORBITOL 2 g/100 g; DODECYL BENZENE SULFONATE DIETHANOLAMINE (MIXED ISOMERS) 3 g/100 g; PROPYLENE GLYCOL 1 g/100 g; SODIUM HYDROXIDE 0.675 g/100 g; WATER 86.325 g/100 g

05%/5% Elite Barrier Dip

Summary of effectiveness

Helps reduce the spread of organisms which may
cause Mastitis

Instructions for Use

USE DIRECTIONS: NOT FOR HUMAN USE
FOR EXTERNAL USE ONLY
USE AT FULL STRENGTH

Safe Handling

CAUTION
KEEP OUT OF REACH OF CHILDREN
NOT FOR HUMAN USE

General Precautions

Avoid eye contact. Do not ingest.Do not mix with any chemicals except as directed.

Storage

Store in a closed container away from sources of heat. If product becomes frozen, thaw and mix well before
use.

label